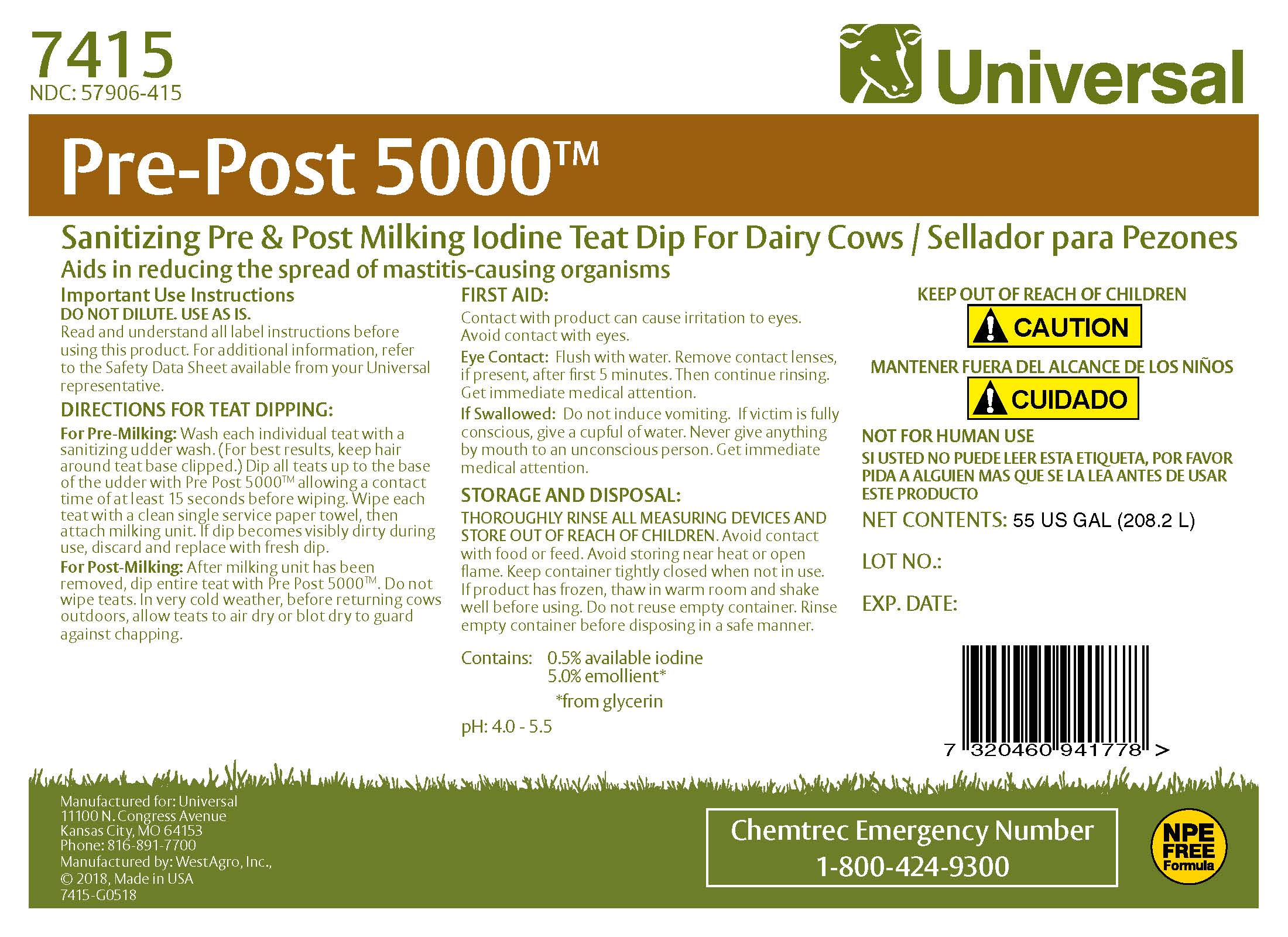 DRUG LABEL: Pre Post 5000
NDC: 57906-415 | Form: SOLUTION
Manufacturer: Universal
Category: animal | Type: OTC ANIMAL DRUG LABEL
Date: 20230216

ACTIVE INGREDIENTS: IODINE 5.1 g/1 L

Universal Pre-Post 5000

7415

NDC: 57906-415

INDICATIONS AND USAGE

Sanitizing Pre and Post Milking Iodine Teat Dip for Dairy Cows / Sellador para Pezones

Important Use Instructions
DO NOT DILUTE. USE AS IS.
Read and understand all label instructions before using this product. For additional information, refer to the Material Safety Data Sheet available from your Universal representative.
DIRECTIONS FOR TEAT DIPPING
FOR PRE-MILKING:
Wash each individual teat with a sanitizing udder wash. (For best results, keep hair around teat base clipped.) Dip all teats up to the base of the udder with PRE POST 5000 allowing a contact time of at least 15 seconds before wiping. Wipe each teat with a clean single service paper towel, then attach milking unit. If dip becomes visibly dirty during use, discard and replace with fresh dip.
FOR POST-MILKING:
After milking unit has been removed, dip entire teat with PRE POST 5000. Do not wipe teats. In very cold weather, before returning cows outdoors, allow teats to air dry or blot dry to guard against chapping.

FIRST AID
Contact with product can cause irritation to eyes. Keep out of eyes.
Eye Contact: Flush with water. Remove contact lenses after first 5 minutes, if present, then continue flushing.
If Swallowed: Drink large quantities of water and induce vomiting.

STORAGE AND DISPOSAL:
THOROUGHLY RINSE ALL MEASURING DEVICES AND STORE OUT OF REACH OF CHILDREN. Avoid contact with food or feed. Avoid storing near heat or open flame. Keep container tightly closed when not in use. If product has frozen, thaw in warm room and shake well before using. Do not reuse empty container. Rinse empty container before disposing in a safe manner.

KEEP OUT OF REACH OF CHILDREN

MANTENER FUERA DEL ALCANCE DE LOS NINOS

! CAUTION !CUIDADO

SI USTED NO PUEDE LEER ESTA ETIQUETA, POR FAVOR PIDA A ALGUIEN MAS QUE SE LA LEA ANTES DE USAR ESTE PRODUCTO

ACTIVE INGREDIENT

Contains: 0.5% available iodine with an emollient system
pH: 4.0-5.5

Net Contents:
Lot No.:
Exp. Date:

Manufactured for: Universal
11100 N. Congress Avenue
Kansas City, MO 64153
Phone: 816-891-7700
Manufactured by: WestAgro, Inc.
©2018, Made in USA

Chemtrec Emergency Number
1-800-424-9300

NPE FREE Formula